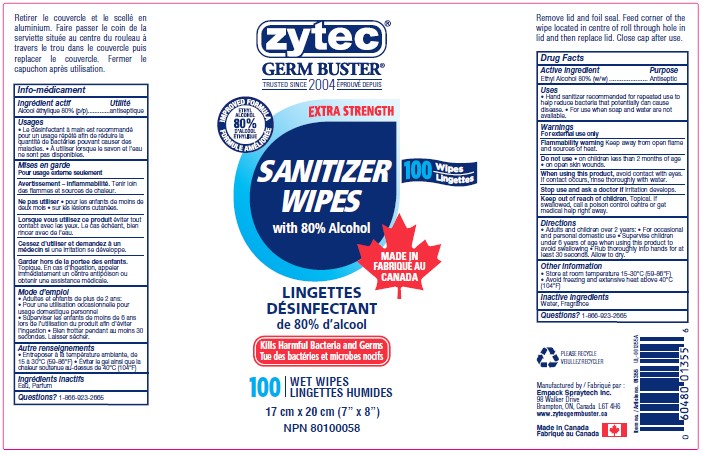 DRUG LABEL: Zytec Hand Sanitizer Wipes
NDC: 50021-014 | Form: CLOTH
Manufacturer: Empack Spraytech Inc.
Category: otc | Type: HUMAN OTC DRUG LABEL
Date: 20241212

ACTIVE INGREDIENTS: ALCOHOL 80 g/100 g
INACTIVE INGREDIENTS: WATER; FRAGRANCE LEMON ORC2001060

50021-014 Zytec Hand Sanitizer Wipes

This is a hand sanitizer wipes Alcohol 80% w/w

Active Ingredient(s)

Alcohol Wipes 80% w/w. Purpose: Antiseptic

Purpose

Antiseptic, Hand Sanitizer

Use

Hand Sanitizer to help reduce bacteria that potentially can cause disease. For use when soap and water are not available.

Warnings

For external use only. Flammable. Keep away from heat or flame

Do not use

- in children less than 2 months of age
- on open skin wounds

When using this product keep out of eyes, ears, and mouth. In case of contact with eyes, rinse eyes thoroughly with water.
Stop use and ask a doctor if irritation or rash occurs. These may be signs of a serious condition.
Keep out of reach of children. If swallowed, get medical help or contact a Poison Control Center right away.

Stop use and ask a doctor if irritation or rash occurs. These may be signs of a serious condition.

Keep out of reach of children. If swallowed, get medical help or contact a Poison Control Center right away.

Directions

- Wet hands thoroughly with product for 30 seconds and allow to dry without wiping. Discard after single use, do not flush in toilet.
- Supervise children under 6 years of age when using this product to avoid swallowing.

Other information

- Store between 15-30C (59-86F)
- Avoid freezing and excessive heat above 40C (104F)

Inactive ingredients

Water (Aqua), Fragrance (Aqua).

Package Label - Principal Display Panel

Hand Sanitizer Wipe 80% w/w Alcohol